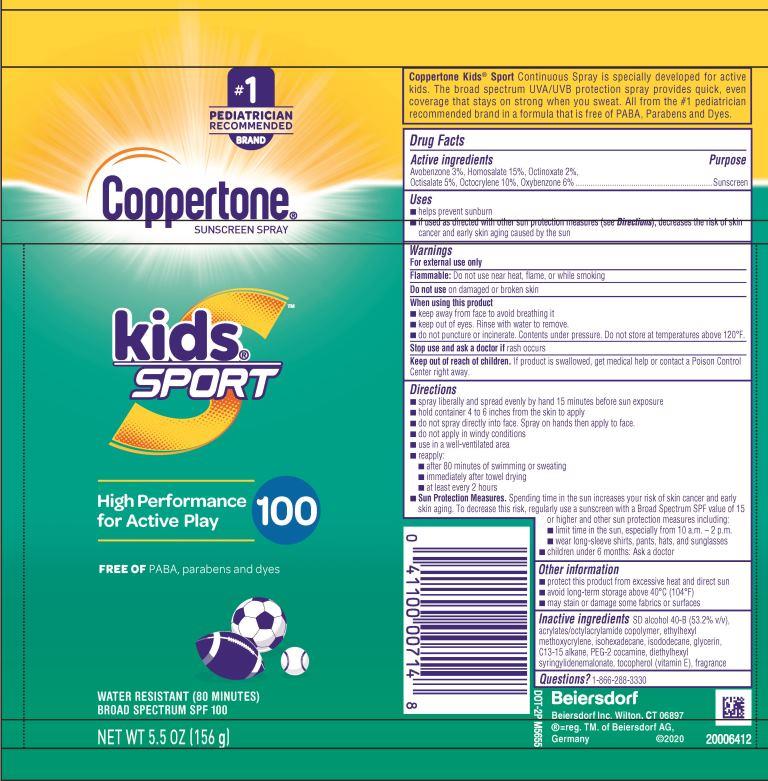 DRUG LABEL: Coppertone Kids Sport Sunscreen SPF 100
NDC: 66800-2495 | Form: SPRAY
Manufacturer: Beiersdorf Inc
Category: otc | Type: HUMAN OTC DRUG LABEL
Date: 20251231

ACTIVE INGREDIENTS: OCTOCRYLENE 10 g/100 g; OXYBENZONE 6 g/100 g; OCTINOXATE 2 g/100 g; AVOBENZONE 3 g/100 g; HOMOSALATE 15 g/100 g; OCTISALATE 5 g/100 g
INACTIVE INGREDIENTS: ISOHEXADECANE; ISODODECANE; GLYCERIN; ALCOHOL; ETHYLHEXYL METHOXYCRYLENE; C13-15 ALKANE; PEG-3 COCAMINE; DIETHYLHEXYL SYRINGYLIDENEMALONATE; TOCOPHEROL; FRAGRANCE FLORAL ORC0902236; ACRYLATES CROSSPOLYMER-6; OCTYL ACRYLATE

Kids Sport Spray SPF 100

Active ingredients

Avobenzone 3%, Homosalate 15%, Octinoxate 2%, Octisalate 5%, Octocrylene 10%, Oxybenzone 6%

Purpose

Sunscreen

Uses

■ helps prevent sunburn

■ if used as directed with other sun protection measures (see Directions), decreases the risk of skin cancer and early skin aging caused the the sun

Warnings

For external use only

Flammable:Do not use near heat, flame, or while smoking

Do not useon damaged or broken skin

When using this product
■ keep away from face to avoid breathing it

■ keep out of eyes. Rinse with water to remove.

■ do not puncture or incinerate. Contents under pressure. Do not store at temperatures above 120˚F.

Stop use and ask a doctor ifrask occurs

Keep out of reach of children.If product is swallowed, get medical help or contact a Poison Control Center right away.

Directions

■ spray liberally and spread evenly by hand 15 minutes before sun exposure

■ hold container 4 to 6 inches from the skin to apply

■ do not spray directly into face. Spray on hands then apply to face.

■ do not apply in windy conditions

■ use in a well-ventilated area

■ reapply:

■ after 80 minutes of swimming or sweating

■ immediately after towel drying

■ at least every 2 hours

■ Sun Protection Measures.Spending time in the sun increases your risk of skin cancer and early skin aging. To decrease this risk, regularly use a sunscreen with a Broad Spectrum SPF value of 15 or higher and other sun protection measures including:

■ limit time in the sun, especially from 10 a.m. – 2 p.m.

■ wear long-sleeve shirts, pants, hats, and sunglasses

■ children under 6 months: Ask a doctor

Other information

■ protect this product from excessive heat and direct sun

■ avoid long-term storage above 40˚C (104˚F)

■ may stain or damage some fabrics or surfaces

Inactive ingredients

SD alcohol 40-B (53.2% v/v), acrylates/octylacrylamide copolymer, ethylhexyl methoxycrylene, isohexadecane, isododecane, glycerin, C13-15 alkane, PEG-2 cocamine, diethylhexyl syringylidenemalonate, tocopherol (vitamin E), fragrance

Questions

1-866-288-3330

PACKAGE LABEL

#1 Pediatrician Recommended Brand

Coppertone®Sunscreen Spray

kids Sport

High Performance for Active Play 100

Free of PABA, parabens and dyes

Water Resistant (80 Minutes)

Broad Specturm SPF 100

Net Wt 5.5 OZ (156 g)